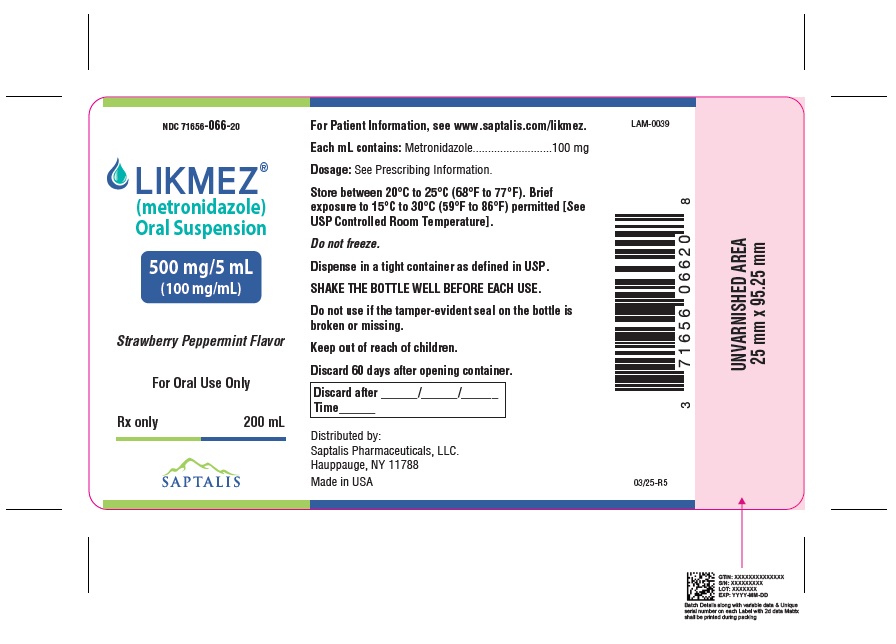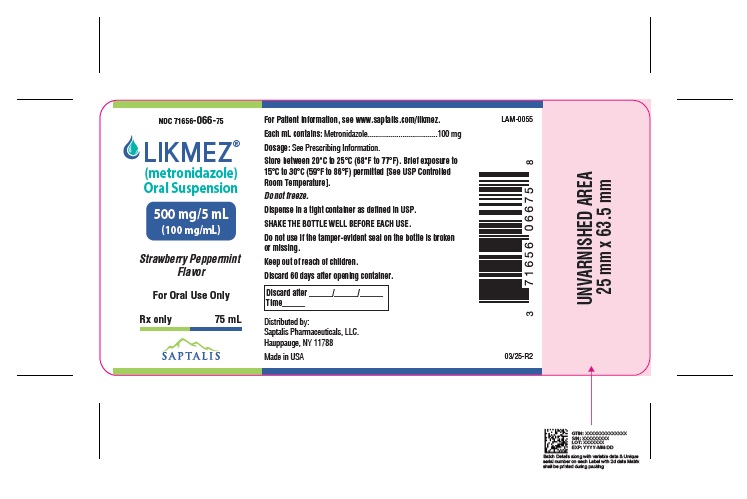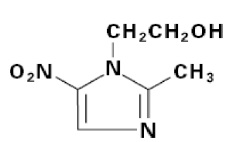 DRUG LABEL: LIKMEZ
NDC: 71656-066 | Form: SUSPENSION
Manufacturer: Saptalis Pharmaceuticals, LLC
Category: prescription | Type: HUMAN PRESCRIPTION DRUG LABEL
Date: 20250418

ACTIVE INGREDIENTS: METRONIDAZOLE 100 mg/1 mL
INACTIVE INGREDIENTS: GLYCERIN; MAGNESIUM ALUMINUM SILICATE; METHYLPARABEN; MICROCRYSTALLINE CELLULOSE; PEPPERMINT; PROPYLPARABEN; WATER; SODIUM PHOSPHATE DIBASIC DIHYDRATE; SODIUM PHOSPHATE, MONOBASIC; STRAWBERRY; SUCRALOSE; SUCROSE

HIGHLIGHTS OF PRESCRIBING INFORMATION

These highlights do not include all the information needed to use LIKMEZ safely and effectively. See full prescribing information for LIKMEZ.
LIKMEZ™ (metronidazole) oral suspension
Initial U.S. Approval: 1963

WARNING: POTENTIAL FOR CARCINOGENICITY

See full prescribing information for complete boxed warning.

Metronidazole has been shown to be carcinogenic in mice and rats (5.1). Avoid unnecessary use of LIKMEZ. Reserve LIKMEZ for use in the following indications: trichomoniasis (1.1), amebiasis (1.2) and anaerobic bacterial infections (1.3).

RECENT MAJOR CHANGES

Severe Cutaneous Adverse Reactions (5.2) 7/2024

1 INDICATIONS AND USAGE

LIKMEZ is a nitroimidazole antimicrobial indicated for

- Trichomoniasis in adults (1.1)
- Amebiasis in adults and pediatric patients (1.2)
- Anaerobic Bacterial Infections in adults (1.3)

To reduce the development of drug-resistant bacteria and maintain the effectiveness of LIKMEZ and other antibacterial drugs, LIKMEZ should be used only to treat or prevent infections that are proven or strongly suspected to be caused by bacteria (1.4).

2 DOSAGE AND ADMINISTRATION

Trichomoniasis:

Adult Female and Male Patients:

- One-day treatment: 2 g (20 mL) of LIKMEZ, given either as a single oral dose or in 2 divided oral doses of 1 g (10 mL) each, given on the same day. (2.1)
- Seven-day course of treatment: 250 mg (2.5 mL) of LIKMEZ given three times daily for 7 consecutive days. (2.1)
- Individualize the dosing regimen. (2.1)

Amebiasis:

Adult Patients:

- For acute intestinal amebiasis (acute amebic dysentery):750 mg (7.5 mL) orally three times daily for 5 days to 10 days. (2.2)
- For amebic liver abscess:500 mg (5 mL) or 750 mg (7.5 mL) orally three times daily for 5 days to 10 days. (2.2)

Pediatric Patients:35 mg/kg/24 hours to 50 mg/kg/24 hours, divided into three doses, to a maximum dose of 2,250 mg/24 hours (maximum dose 750 mg/dose or 7.5 mL/dose), orally for 10 days. (2.2)

Anaerobic Bacterial Infections:

- In the treatment of most serious anaerobic infections, intravenous metronidazole is usually administered initially. (2.3)
- Adult Patients:7.5 mg/kg every six hours (approx. 500 mg (5 mL) for a 70-kg adult) to a maximum dose of 4 g (40 mL) during a 24-hour period, orally for 7 to 10 days. (2.3)
- Infections of the bone and joint, lower respiratory tract, and endocardium may require longer treatment. (2.3)

Patients with Severe Hepatic Impairment (Child-Pugh C)

- Reduce the dose of LIKMEZ by 50%. (2.4)

Patients Undergoing Hemodialysis:

Consider a supplemental dose of LIKMEZ following the hemodialysis session, depending on the patient’s clinical situation. (2.5)

3 DOSAGE FORMS AND STRENGTHS

Oral Suspension:500 mg/5 mL (3)

4 CONTRAINDICATIONS

- Prior history of hypersensitivity to metronidazole or other nitroimidazole derivatives (4.1)
- Patients who have used disulfiram within the last two weeks. (4.2, 7.1)
- Patients who consume alcohol or products containing propylene glycol during and for at least three days after LIKMEZ therapy. (4.3, 7.2)
- Patients with Cockayne syndrome (4.4, 6.2)

5 WARNINGS AND PRECAUTIONS

- Severe Cutaneous Adverse Reactions: Severe cutaneous adverse reactions (SCARs) including toxic epidermal necrolysis (TEN), Stevens-Johnson syndrome (SJS), drug reaction with eosinophilia and systemic symptoms (DRESS), and acute generalized exanthematous pustulosis (AGEP) have been reported with metronidazole. If symptoms or signs of SCARs develop, discontinue LIKMEZ immediately and institute appropriate therapy. (5.2)
- Central and Peripheral Nervous System Effects:Encephalopathy, convulsive seizures, aseptic meningitis and peripheral neuropathy have
  been reported with metronidazole. Promptly evaluate the benefit/risk of continuation of LIKMEZ if abnormal neurological signs develop. (5.3)
- Blood Dyscrasias: Use LIKMEZ with care in patients with a history of blood dyscrasias. LIKMEZ may cause mild transient leukopenia. (5.5)

6 ADVERSE REACTIONS

Common adverse reactions include nausea, headache, anorexia, vomiting, diarrhea, abdominal cramping, epigastric distress, and constipation. (6.1)

To report SUSPECTED ADVERSE REACTIONS, contact Saptalis Pharmaceuticals, LLCat 1-833-727-8254 or FDA at 1-800-FDA-1088 or http://www.fda.gov/medwatch.

7 DRUG INTERACTIONS

- Disulfiram:Psychotic reactions can occur in patients who are using LIKMEZ and disulfiram concurrently. (4.2, 7.1)
- Alcohol or Other Products Containing Propylene Glycol:Abdominal cramps, nausea, vomiting, headaches, and flushing can occur in patients who are using LIKMEZ and alcohol or other products containing propylene glycol concurrently. (4.3, 7.2)
- Warfarin and Other Oral Anticoagulants: LIKMEZ can potentiate the anticoagulant effect. Carefully monitor prothrombin time and International Normalized Ratio (INR). (7.3)
- Lithium:Increased lithium serum concentrations; measure serum lithium and serum creatinine concentrations during therapy. (7.4)
- Busulfan: Increased busulfan serum concentrations; avoid concomitant use, monitor for plasma concentrations and adjust the busulfan dose accordingly. (7.5)
- CYP Inducers and CYP Inhibitors: Prolonged or accelerated half-life of metronidazole or concomitant medications. (7.6, 7.7)
- Drugs with the Potential for Prolonging the QT Interval:QT prolongation when used with LIKMEZ (7.8)
- Interference with Laboratory Tests:Metronidazole may interfere with certain serum chemistry laboratory values (7.9)

8 USE IN SPECIFIC POPULATIONS

Lactation: A lactating woman may choose to pump and discard human milk for the duration of LIKMEZ therapy and for 48 hours after the last dose and feed her infant stored human milk or formula. (8.2)

FULL PRESCRIBING INFORMATION

WARNING: POTENTIAL FOR CARCINOGENICITY

Metronidazole has been shown to be carcinogenic in mice and rats. [see Warnings and Precautions (5.1)] . Avoid unnecessary use of LIKMEZ. Reserve LIKMEZ for use in the following indications: trichomoniasis [see Indications and Usage (1.1)] , amebiasis [see Indications and Usage (1.2)] and anaerobic bacterial infections [see Indications and Usage (1.3)].

RECENT MAJOR CHANGES

Severe Cutaneous Adverse Reactions (5.2)7/2024

1 INDICATIONS AND USAGE

1.1 Trichomoniasis

LIKMEZ is indicated for the treatment of:

- Symptomatic trichomoniasis caused by Trichomonas vaginalis in adult females and males when the diagnosis is confirmed by appropriate laboratory procedures.
- Asymptomatic trichomoniasis caused by Trichomonas vaginalis in adult females when the organism is associated with endocervicitis, cervicitis, or cervical erosion.

Because trichomoniasis is a sexually transmitted disease with potentially serious sequelae, treat sexual partners of patients simultaneously to prevent re-infection.

1.2 Amebiasis

LIKMEZ is indicated for the treatment of acute intestinal amebiasis (amoebic dysentery) and amebic liver abscess in adults and pediatric patients. In amebic liver abscess, treatment with LIKMEZ does not obviate the need for aspiration or drainage of pus.

1.3 Anaerobic Bacterial Infections

LIKMEZ is indicated in the treatment of the following serious infections caused by susceptible anaerobic bacteria in adults:

- Intra-abdominal infections, including peritonitis, intra-abdominal abscess, and liver abscess, caused by Bacteroides species including the B. fragilis group (B. fragilis, B. ovatus, B. thetaiotaomicron, B. vulgatus), Parabacteroides distasonis, Clostridium species, Eubacterium species, Peptococcus species,and Peptostreptococcus species.
- Skin and skin structure infections caused by Bacteroides species including the B. fragilis group, Clostridium species, Peptococcus species, Peptostreptococcus species, and Fusobacterium species.
- Gynecologic infections, including endometritis, endomyometritis, tubo-ovarian abscess, and postsurgical vaginal cuff infection, caused by Bacteroides species including the B. fragilis group, Clostridium species, Peptococcus species, Peptostreptococcus species, and Fusobacterium species.
- Bacterial septicemia caused by Bacteroides species including the B. fragilis group and Clostridiums pecies.
- Bone and joint infections, (as adjunctive therapy), caused by Bacteroides species including the B. fragilis group.
- Central nervous system (CNS) infections, including meningitis and brain abscess, caused by Bacteroides species including the B. fragilis group.
- Lower respiratory tract infections, including pneumonia, empyema, and lung abscess, caused by Bacteroides species including the B. fragilis group.
- Endocarditis caused by Bacteroides species including the B. fragilis group.

Indicated surgical procedures should be performed in conjunction with LIKMEZ therapy. In a mixed aerobic and anaerobic infection, antimicrobials appropriate for the treatment of aerobic infection should be used in addition to LIKMEZ.

1.4 Usage

To reduce the development of drug-resistant bacteria and maintain the effectiveness of LIKMEZ and other antibacterial drugs, LIKMEZ should be used only to treat or prevent infections that are proven or strongly suspected to be caused by susceptible bacteria. When culture and susceptibility information are available, they should be considered in selecting or modifying antibacterial therapy. In the absence of such data, local epidemiology and susceptibility patterns may contribute to the empiric selection of therapy.

2 DOSAGE AND ADMINISTRATION

2.1 Recommended Dosage for Trichomoniasis

Adult Female and Male Patients:

- One-day Treatment–Administer 2 g (20 mL) of LIKMEZ, either as a single oral dose or in 2 divided oral doses of 1 g (10 mL) each, given on the same day.
- Seven-day Course of Treatment−Administer 250 mg (2.5 mL) of LIKMEZ orally 3 times daily for 7 consecutive days.

The dosage regimen should be individualized. Single-dose treatment may help improve compliance, especially if administered under supervision, in those patients who cannot be relied on to continue the seven-day regimen.

A seven-day course of treatment may minimize reinfection by protecting the patient long enough for the sexual contacts to obtain appropriate treatment. There are some data from controlled comparative studies that cure rates as determined by vaginal smears and signs and symptoms, may be higher after a seven-day course of treatment than after a one-day treatment regimen. Further, some patients may tolerate one treatment regimen better than the other.

When repeat courses of LIKMEZ are required, it is recommended that an interval of four to six weeks elapse between courses and that the presence of the trichomonad be reconfirmed by appropriate laboratory measures. Total and differential leukocyte counts should be made before and after re-treatment.

2.2 Recommended Dosage for Amebiasis

Adult Patients:

- For acute intestinal amebiasis (acute amebic dysentery):Administer 750 mg (7.5 mL) of LIKMEZ orally three times daily for 5 days to 10 days.
- For amebic liver abscess:Administer 500 mg (5 mL) or 750 mg (7.5 mL) of LIKMEZ orally three times daily for 5 days to 10 days.

Pediatric Patients:

- Administer 35 mg/kg/24 hours to 50 mg/kg/24 hours of LIKMEZ, divided into three doses, to a maximum dose of 2,250 mg/24 hours (maximum dose 750 mg/dose or 7.5 mL/dose), orally for 10 days.

2.3 Recommended Dosage for Anaerobic Bacterial Infections

In the treatment of most serious anaerobic infections, intravenous metronidazole is usually administered initially.

Adult Patients: Administer 7.5 mg/kg of LIKMEZ orally every six hours (approx. 500 mg (5 mL) for a 70 kg adult) for 7 days to 10 days. Infections of the bone and joint, lower respiratory tract, and endocardium may require longer treatment.

Do not exceed a maximum of 4 g (40 mL) during a 24-hour period.

2.4 Recommended Dosage in Patients with Severe Hepatic Impairment

For patients with severe hepatic impairment (Child-Pugh C), reduce the dose of LIKMEZ by 50% [see Use in Specific Populations (8.7)and Clinical Pharmacology (12.3)].

2.5 Recommended Dosage in Patients Undergoing Hemodialysis

Hemodialysis removes significant amounts of metronidazole and its metabolites from systemic circulation. The clearance of metronidazole will depend on the type of dialysis membrane used, the duration of the dialysis session, and other factors. If the administration of LIKMEZ cannot be separated from the hemodialysis session, consider a supplemental dose of LIKMEZ following the hemodialysis session, depending on the patient’s clinical situation [see Clinical Pharmacology (12.3)] .

No adjustment in LIKMEZ dose is needed in patients undergoing continuous ambulatory peritoneal dialysis (CAPD) [see Clinical Pharmacology (12.3)] .

2.6 Important Administration Instructions

Shake the bottle well before administering the recommended dosage.

Use a calibrated oral dosing device to correctly measure the prescribed dose of medication. Do not use household teaspoons or tablespoons to measure doses. Calibrated oral dosing devices may be obtained from the pharmacy.

3 DOSAGE FORMS AND STRENGTHS

Oral Suspension:500 mg/5 mL white to slightly brown suspension with a characteristic strawberry peppermint flavor.

4 CONTRAINDICATIONS

4.1 Hypersensitivity Reactions

LIKMEZ is contraindicated in patients with known hypersensitivity to metronidazole or other nitroimidazole derivatives [see Adverse Reactions (6.1)] .

4.2 Psychotic Reactions with Disulfiram

LIKMEZ is contraindicated in patients who have used disulfiram within the last two weeks. Use of oral metronidazole is associated with psychotic reactions in alcoholic patients who were using disulfiram concurrently [see Drug Interactions (7.1)] .

4.3 Interaction with Alcohol

LIKMEZ is contraindicated in patients who consume alcohol or products containing propylene glycol during and for at least three days after LIKMEZ therapy. Use of oral metronidazole is associated with a disulfiram-like reaction to alcohol, including abdominal cramps, nausea, vomiting, headaches, and flushing [see Drug Interactions (7.2)] .

4.4 Cockayne Syndrome

LIKMEZ is contraindicated in patients with Cockayne syndrome. Severe irreversible hepatotoxicity/acute liver failure with fatal outcomes have been reported after initiation of metronidazole in patients with Cockayne syndrome [see Adverse Reactions (6.2)] .

5 WARNINGS AND PRECAUTIONS

5.1 Potential for Carcinogenicity

Metronidazole has been shown to be carcinogenic in mice and rats. Tumors affecting the liver, lungs, mammary, and lymphatic tissues have been detected in several studies of metronidazole in rats and mice, but not hamsters [see Nonclinical Toxicology (13.1)] . Avoid unnecessary use of LIKMEZ. Reserve LIKMEZ for use in the following indications: trichomoniasis [see Indications and Usage (1.1)] , amebiasis [see Indications and Usage (1.2)] and anaerobic bacterial infections [see Indications and Usage (1.3)].

5.2 Severe Cutaneous Adverse Reactions

Severe cutaneous adverse reactions (SCARs) including toxic epidermal necrolysis (TEN), Stevens-Johnson syndrome (SJS), drug reaction with eosinophilia and systemic symptoms (DRESS), and acute generalized exanthematous pustulosis (AGEP) have been reported with the use of metronidazole. Symptoms can be serious and potentially life threatening. If symptoms or signs of SCARs develop, discontinue LIKMEZ immediately and institute appropriate therapy.

5.3 Central and Peripheral Nervous System Effects

Encephalopathy, aseptic meningitis, peripheral neuropathy (including optic neuropathy) and convulsive seizures have been reported with metronidazole. Encephalopathy has been reported in association with cerebellar toxicity characterized by ataxia, dizziness, and dysarthria. CNS lesions seen on MRI have been described in reports of encephalopathy. CNS symptoms are generally reversible within days to weeks upon discontinuation of metronidazole. CNS lesions seen on MRI have also been described as reversible. Peripheral neuropathy, mainly of sensory type has been reported and is characterized by numbness or paresthesia of an extremity. Cases of aseptic meningitis have been reported with metronidazole [ see Adverse Reactions (6.1)]. Symptoms may occur within hours of dose administration and generally resolve after metronidazole therapy is discontinued. The appearance of abnormal neurological signs and symptoms demands the prompt evaluation of the benefit/risk ratio of the continuation of therapy.

5.4 Fungal Superinfections

Known or previously unrecognized candidiasis may present more prominent symptoms during therapy with LIKMEZ and requires treatment with an antifungal agent.

5.5 Blood Dyscrasias

LIKMEZ is a nitroimidazole and should be used with care in patients with evidence of or history of blood dyscrasia. A mild leukopenia has been observed during metronidazole administration; however, no persistent hematologic abnormalities attributable to metronidazole have been observed in clinical studies. Total and differential leukocyte counts are recommended before and after therapy [see Adverse Reactions (6.1)] .

5.6 Drug-Resistant Bacteria

Prescribing LIKMEZ in the absence of a proven or strongly suspected bacterial infection or a prophylactic indication is unlikely to provide benefit to the patient and increases the risk of thedevelopment of drug-resistant bacteria.

6 ADVERSE REACTIONS

The following clinically significant adverse reactions are described elsewhere in the labeling:

- Severe Cutaneous Adverse Reactions [ see Warnings and Precautions (5.2)]
- Central and Peripheral Nervous System Effects [see Warnings and Precautions (5.2)]
- Blood Dyscrasias [see Warnings and Precautions (5.5)]

6.1 Clinical Trials Experience

Because clinical trials are conducted under widely varying conditions, adverse reaction rates observed in the clinical trials of a drug cannot be directly compared to rates in the clinical trials of another drug and may not reflect the rates observed in practice.

The following reactions have been reported during treatment with metronidazole:

Central and Peripheral Nervous System: The most serious adverse reactions reported in patients treated with metronidazole have been convulsive seizures, encephalopathy, aseptic meningitis, optic and peripheral neuropathy, the latter characterized mainly by numbness or paresthesia of an extremity. Persistent peripheral neuropathy has been reported in some patients receiving prolonged administration of metronidazole. In addition, headache, syncope, dizziness, vertigo, incoordination, ataxia, confusion, dysarthria, irritability, depression, weakness, and insomnia have been reported.

Gastrointestinal: The most common adverse reactions reported have been referable to the gastrointestinal tract, particularly nausea, sometimes accompanied by headache, anorexia, and occasionally vomiting; diarrhea; epigastric distress; and abdominal cramping and constipation.

Mouth: A sharp, unpleasant metallic taste is not unusual. Furry tongue, glossitis, and stomatitis have occurred; these may be associated with a sudden overgrowth of Candidawhich may occur during therapy.

Dermatologic: Erythematous rash and pruritus.

Hematopoietic: Reversible neutropenia (leukopenia); reversible thrombocytopenia.

Cardiovascular: QT prolongation has been reported, particularly when metronidazole was administered with drugs with the potential for prolonging the QT interval. Flattening of the T‑wave may be seen in electrocardiographic tracings.

Hypersensitivity: Urticaria, erythematous rash, Stevens-Johnson Syndrome, toxic epidermal necrolysis, flushing, nasal congestion, dryness of the mouth (or vagina or vulva), and fever.

Renal: Dysuria, cystitis, polyuria, incontinence, and a sense of pelvic pressure. Instances of darkened urine have been reported by approximately one patient in 100,000. Although the pigment which is probably responsible for this phenomenon has not been positively identified, it is almost certainly a metabolite of metronidazole and seems to have no clinical significance.

Other: Proliferation of Candidain the vagina, dyspareunia, decrease of libido, proctitis, and fleeting joint pains sometimes resembling “serum sickness.” Cases of pancreatitis, which generally abated on withdrawal of the drug, have been reported.

Patients with Crohn’s disease are known to have an increased incidence of gastrointestinal and certain extraintestinal cancers. There have been some reports in the medical literature of breast and colon cancer in Crohn’s disease patients who have been treated with metronidazole at high doses for extended periods of time. A cause-and-effect relationship has not been established. Crohn’s disease is not an approved indication for LIKMEZ.

6.2 Postmarketing Experience

The following adverse reactions have been identified during post-approval use of metronidazole. Because these reactions are reported voluntarily from a population of uncertain size, it is not always possible to reliably estimate their frequency or establish a causal relationship to drug exposure.

The cases of severe irreversible hepatotoxicity/acute liver failure, including cases with fatal outcomes with very rapid onset after initiation of systemic use of metronidazole have been reported in patients with Cockayne syndrome (latency from drug start to signs of liver failure as short as 2 days) [ see Contraindications (4.4)] .

Central and Peripheral Nervous System: Tinnitus, hearing impairment, and hearing loss.

Hypersensitivity: Drug reaction with eosinophilia and systemic symptoms (DRESS), acute generalized exanthematous pustulosis (AGEP) [ see Warnings and Precautions (5.2)] .

7 DRUG INTERACTIONS

7.1 Disulfiram

Psychotic reactions have been reported in alcoholic patients who are using metronidazole and disulfiram concurrently. LIKMEZ is contraindicated in patients who have taken disulfiram within the last two weeks [see Contraindications (4.2)] .

7.2 Alcoholic Beverages

LIKMEZ is contraindicated in patients who consume alcohol or products containing propylene glycol during and for at least 3 days after therapy with LIKMEZ. Use of LIKMEZ with alcohol or other products containing propylene glycol is associated with a disulfiram-like reaction (abdominal cramps, nausea, vomiting, headaches, and flushing) [see Contraindications (4.3)] .

7.3 Warfarin and other Oral Anticoagulants

Metronidazole has been reported to potentiate the anticoagulant effect of warfarin and other oral coumarin anticoagulants, resulting in a prolongation of prothrombin time. When LIKMEZ is prescribed for patients on this type of anticoagulant therapy, prothrombin time and INR should be carefully monitored.

7.4 Lithium

In patients stabilized on relatively high doses of lithium, short-term use of LIKMEZ has been associated with elevation of serum lithium concentrations and signs of lithium toxicity due to the interaction between metronidazole and lithium. Monitor serum lithium and serum creatinine concentrations for several days after beginning treatment with LIKMEZ to detect any increase that may precede clinical symptoms of lithium toxicity.

7.5 Busulfan

Metronidazole has been reported to increase plasma concentrations of busulfan, which can result in an increased risk for serious busulfan toxicity. Do not administer LIKMEZ concomitantly with busulfan unless the benefit outweighs the risk. If no therapeutic alternatives to LIKMEZ are available, and concomitant administration with busulfan is medically needed, monitor for busulfan plasma concentrations and adjust the busulfan dose accordingly.

7.6 Inhibitors of CYP450 Liver Enzymes

The simultaneous administration of LIKMEZ and drugs that decrease microsomal liver enzymes, such as cimetidine, may prolong the half-life and decrease plasma clearance of metronidazole.

7.7 Inducers of CYP450 Liver Enzymes

The simultaneous administration of LIKMEZ and drugs that induce microsomal liver enzymes, such as phenytoin or phenobarbital, may accelerate the elimination of metronidazole, resulting in reduced plasma concentrations of metronidazole. Impaired clearance of phenytoin has also been reported.

7.8 Drugs that Prolong the QT Interval

QT prolongation has been reported, particularly when metronidazole was administered with drugs with the potential for prolonging the QT interval.

7.9 Drug/Laboratory Test Interactions

Metronidazole may interfere with certain types of determinations of serum chemistry values, such as aspartate aminotransferase (AST, SGOT), alanine aminotransferase (ALT, SGPT), lactate dehydrogenase (LDH), triglycerides, and glucose hexokinase. Values of zero may be observed. All of the assays in which interference has been reported involve enzymatic coupling of the assay to oxidation-reduction of nicotinamide adenine dinucleotide (NAD^+⇌ NADH). Interference is due to the similarity in absorbance peaks of NADH (340 nm) and metronidazole (322 nm) at pH 7.

8 USE IN SPECIFIC POPULATIONS

8.1 Pregnancy

Risk Summary

While available studies cannot definitively establish the absence of risk, published data from case-control studies, cohort studies and meta-analyses have not established an association with metronidazole use during pregnancy and major birth defects, miscarriage or other adverse maternal or fetal outcomes (see Data).

The background risk of major birth defects and miscarriage for the indicated population is unknown. All pregnancies have a background risk of birth defect, loss, or other adverse outcomes. In the U.S. general population, the estimated background risk of major birth defects and miscarriage in clinically recognized pregnancies is 2% to 4% and 15% to 20%, respectively.

Data

Human Data

There are published data from case-control studies, cohort studies, and 2 meta-analyses that include more than 5,000 pregnant women who used metronidazole during pregnancy. Many studies included first trimester exposures. One study showed an increased risk of cleft lip, with or without cleft palate, in infants exposed to metronidazole in-utero; however, these findings were not confirmed. In addition, more than ten randomized, placebo-controlled clinical trials enrolled more than 5,000 pregnant women to assess the use of antibiotic treatment (including metronidazole) for bacterial vaginosis on the incidence of preterm delivery. Most studies did not show an increased risk for congenital anomalies or other adverse fetal outcomes following metronidazole exposure during pregnancy. Three studies conducted to assess the risk of infant cancer following metronidazole exposure during pregnancy did not show an increased risk; however, the ability of these studies to detect such a signal was limited.

Animal Data

Metronidazole crosses the placental barrier. Reproduction studies have been performed in rats, rabbits, and mice at doses similar to the maximum recommended human dose based on body surface area comparisons. There was no evidence of harm to the fetus due to metronidazole.

8.2 Lactation

Risk Summary

Metronidazole is present in human milk at concentrations similar to maternal serum levels, and infant serum levels can be close to or comparable to infant therapeutic levels. There are no data on the effects of metronidazole on milk production. Animal studies have shown the potential for tumorigenicity after oral metronidazole was administered chronically to rats and mice [see Nonclinical Toxicology (13.1)]. This drug is not intended to be administered chronically; therefore, the clinical relevance of the findings of the animal studies is unclear.

The developmental and health benefits of breastfeeding should be considered along with the mother’s clinical need for LIKMEZ and any potential adverse effects on the breastfed infant from LIKMEZ or from the underlying maternal condition. Alternatively, a lactating woman may choose to pump and discard human milk for the duration of LIKMEZ therapy, and for 48 hours after the last dose and feed her infant stored human milk or formula.

8.4 Pediatric Use

The safety and effectiveness of LIKMEZ for the treatment of amebiasis have been established in pediatric patients.

The safety and effectiveness of LIKMEZ for the treatment of trichomoniasis and anaerobic bacterial infections have not been established in pediatric patients.

8.5 Geriatric Use

In elderly geriatric patients, monitoring for LIKMEZ associated adverse reactions is recommended [see Clinical Pharmacology (12.3)] . Decreased liver function in geriatric patients can result in increased concentrations of metronidazole that may necessitate adjustment of metronidazole dosage [see Dosage and Administration (2.4)].

8.6 Renal Impairment

Patients with end-stage renal disease may excrete metronidazole and metabolites slowly in the urine, resulting in significant accumulation of metronidazole metabolites. Monitor for LIKMEZ associated adverse reactions [see Clinical Pharmacology (12.3)] .

8.7 Hepatic Impairment

Patients with hepatic impairment metabolize metronidazole slowly, with resultant accumulation of metronidazole in the plasma. For patients with severe hepatic impairment (Child-Pugh C), reduce the dose of LIKMEZ by 50%. For patients with mild to moderate hepatic impairment, no dosage adjustment is needed but these patients should be monitored for LIKMEZ associated adverse reactions [ see Clinical Pharmacology (12.3)and Dosage and Administration (2.4)] .

10 OVERDOSAGE

General

Single oral doses of metronidazole, up to 15 g (7.5 times the maximum recommended single dose), have been reported in suicide attempts and accidental overdoses. Symptoms reported include nausea, vomiting, and ataxia. Metronidazole is dialyzable.

Neurotoxic effects, including seizures and peripheral neuropathy, have been reported after 5 days to 7 days of doses of 6 g to 10.4 g every other day (3 times to 5.2 times the maximum recommended single dose).

Treatment of Overdosage

There is no specific antidote for metronidazole overdose; therefore, management of the patient should consist of symptomatic and supportive therapy.

11 DESCRIPTION

LIKMEZ (metronidazole) oral suspension is a nitroimidazole antimicrobial. The chemical name of metronidazole is 2-methyl-5-nitro-1H-imidazole-1-ethanol. The structural formula is shown as:

Metronidazole is a white to pale yellow crystalline powder with a molecular formula of C 6H 9N 3O 3and a molecular weight of 171.2 g/mole. The pKa of metronidazole is 14.44 ± 0.10. The pH of a 1% aqueous solution of metronidazole is 5.5-7.5. It is slightly soluble in water, acetone, alcohol, and methylene chloride.

LIKMEZ is an oral suspension containing 500 mg of metronidazole per 5 mL, and the following inactive ingredients: Glycerin, magnesium aluminum silicate, methylparaben, microcrystalline cellulose, natural peppermint flavor, natural strawberry flavor, propylparaben, purified water, sodium phosphate dibasic, sodium phosphate monobasic, sucralose, and sucrose.

12 CLINICAL PHARMACOLOGY

12.1 Mechanism of Action

Metronidazole is a nitroimidazole antimicrobial drug [see Microbiology (12.4)] .

12.3 Pharmacokinetics

Metronidazole pharmacokinetics are similar for both oral and intravenous dosage forms. The Cmaxis dose proportional between 250 mg, 500 mg, and 2,000 mg for metronidazole oral tablets, producing peak plasma concentrations of 6 mcg/mL, 12 mcg/mL, and 40 mcg/mL, respectively.

Absorption

Following oral administration, LIKMEZ is well absorbed, with peak plasma concentrations occurring between 0.25 and 6 hours after administration.

Two pharmacokinetic studies (Study 1 and Study 2) performed in healthy adult volunteers evaluated the bioavailability of LIKMEZ under fasting and fed conditions.

Effect of Food

Food delays Tmaxand lowers Cmaxwhen compared to fasted conditions, but systemic exposure (AUC) is similar in fed and fasted state (see Table 1).

Table 1: Mean (± S.D.) Pharmacokinetic Parameters Following Single Oral Doses of 500 mg LIKMEZ in Healthy Adults Under Fed and Fasting Conditions
Formulation | Cmax (mcg/mL) | AUC0-∞ (mcg.h/mL) | Tmax [Median (min max)] (h)
Study 1- Fasting state (n = 44)
LIKMEZ | 13 ± 3 | 146 ± 36 | 0.75 (0.25 to 6)
Study 2- Fed State [Fed study administered LIKMEZ following a high-fat, high-calorie breakfast (approximately 1,000 calories, 26.5% carbohydrates, 16.5% protein, and 57% fat).] (n = 46)
LIKMEZ | 10 ± 1 | 144 ± 30 | 2.33 (0.25 to 4)

Distribution

Metronidazole is the major component appearing in the plasma, with lesser quantities of metabolites also being present. Less than 20% of the circulating metronidazole is bound to plasma proteins. Metronidazole appears in cerebrospinal fluid, saliva, and breast milk in concentrations similar to those found in plasma. Bactericidal concentrations of metronidazole have also been detected in pus from hepatic abscesses.

Elimination

Metabolism

The metabolites of metronidazole that appear in the urine result primarily from side-chain oxidation [1-(-hydroxyethyl)-2-hydroxymethyl-5-nitroimidazole and 2-methyl-5-nitroimidazole-1-ylacetic acid] and glucuronide conjugation, with unchanged metronidazole accounting for approximately 20% of the total. Both the parent compound and the hydroxyl metabolite possess in vitroantimicrobial activity.

Excretion

The major route of elimination of metronidazole and its metabolites is via the urine (60% to 80% of the dose), with fecal excretion accounting for 6% to 15% of the dose.

Renal clearance of metronidazole is approximately 10 mL/min/1.73 m^2. The average elimination half-life of LIKMEZ in healthy adult subjects is nine hours.

Specific Populations

Geriatric Patients

Following a single 500 mg oral or IV dose of metronidazole, subjects >70 years old with no apparent renal or hepatic dysfunction had a 40% to 80% higher mean AUC of hydroxy‑metronidazole (active metabolite), with no apparent increase in the mean AUC of metronidazole (parent compound), compared to young healthy controls <40 years old [see Use in Specific Populations (8.5)] .

Pediatric Patients

In one study, newborn infants appeared to demonstrate diminished capacity to eliminate metronidazole. The elimination half-life, measured during the first 3 days of life, was inversely related to gestational age. In infants whose gestational ages were between 28 weeks and 40 weeks, the corresponding elimination half-lives ranged from 109 hours to 22.5 hours.

Male and Female Patients

Studies reveal no significant bioavailability differences between males and females; however, because of weight differences, the resulting plasma levels in males are generally lower.

Patients with Renal Impairment

Decreased renal function does not alter the single-dose pharmacokinetics of metronidazole.

Subjects with end-stage renal disease (ESRD; CLCR= 8.1±9.1 mL/min) and who received a single intravenous infusion of metronidazole 500 mg had no significant change in metronidazole pharmacokinetics but had 2-fold higher Cmaxof hydroxy-metronidazole and 5‑fold higher Cmaxof metronidazole acetate, compared to healthy subjects with normal renal function (CLCR= 126±16 mL/min). Thus, on account of the potential accumulation of metronidazole metabolites in ESRD patients, monitoring for metronidazole associated adverse reactions are recommended [see Use in Specific Populations (8.6)] .

Following a single intravenous infusion or oral dose of metronidazole 500 mg, the clearance of metronidazole was investigated in ESRD subjects undergoing hemodialysis or continuous ambulatory peritoneal dialysis (CAPD). A hemodialysis session lasting for 4 hours to 8 hours removed 40% to 65% of the administered metronidazole dose, depending on the type of dialyzer membrane used and the duration of the dialysis session. If the administration of metronidazole cannot be separated from the dialysis session, supplementation of metronidazole dose following hemodialysis should be considered [see Dosage and Administration (2.5)]. A peritoneal dialysis session lasting for 7.5 hours removed approximately 10% of the administered metronidazole dose. No adjustment in metronidazole dose is needed in ESRD patients undergoing CAPD.

Patients with Hepatic Impairment

Following a single intravenous infusion of 500 mg metronidazole, the mean AUC24of metronidazole was higher by 114% in patients with severe (Child-Pugh C) hepatic impairment, and by 54% and 53% in patients with mild (Child-Pugh A) and moderate (Child-Pugh B) hepatic impairment, respectively, compared to healthy control subjects. There were no significant changes in the AUC24of hydroxyl-metronidazole in these hepatically impaired patients. A reduction in metronidazole dosage by 50% is recommended in patients with severe (Child-Pugh C) hepatic impairment. No dosage adjustment is needed for patients with mild to moderate hepatic impairment. Patients with mild to moderate hepatic impairment should be monitored for metronidazole associated adverse reactions [see Use in Specific Populations (8.7)and Dosage and Administration (2.4)].

12.4 Microbiology

Mechanism of Action

Metronidazole, a nitroimidazole, exerts antibacterial effects in an anaerobic environment against most obligate anaerobes. Once metronidazole enters the organism by passive diffusion and activated in the cytoplasm of susceptible anaerobic bacteria, it is reduced; this process includes intracellular electron transport proteins such as ferredoxin, transfer of an electron to the nitro group of the metronidazole, and formation of a short-lived nitroso free radical. Because of this alteration of the metronidazole molecule, a concentration gradient is created and maintained which promotes the drug’s intracellular transport. The reduced form of metronidazole and free radicals can interact with DNA leading to inhibition of DNA synthesis and DNA degradation leading to death of the bacteria. The precise mechanism of action of metronidazole is unclear.

Resistance

A potential for development of resistance exists against metronidazole.

Resistance may be due to multiple mechanisms that include decreased uptake of the drug, altered reduction efficiency, overexpression of the efflux pumps, inactivation of the drug, and/or increased DNA damage repair.

Metronidazole does not possess any clinically relevant activity against facultative anaerobes or obligate aerobes.

Antimicrobial Activity

Metronidazole has been shown to be active against most isolates of the following microorganisms, both in vitro and in clinical infections [see Indications and Usage (1)].

Gram-positive anaerobes

Clostridiumspecies Eubacterium species

Peptococcus species

Peptostreptococcus species

Gram-negative anaerobes

Bacteroides fragilis group (B. fragilis, B. ovatus, B. thetaiotaomicron, B. vulgatus)

Parabacteroides distasonis

Fusobacterium species

Protozoal parasites

Entamoeba histolytica

Trichomonas vaginalis

The following in vitrodata are available, but their clinical significance is unknown. At least 90 percent of the following bacteria exhibit an in vitro minimum inhibitory concentration (MIC) less than or equal to the susceptible breakpoint for metronidazole against isolates of similar genus or organism group. However, the efficacy of metronidazole in treating clinical infections caused by these bacteria has not been established in adequate and well-controlled clinical trials.

Gram-negative anaerobes

Bacteroides fragilisgroup (B. caccae, B. uniformis)

Prevotellaspecies (P. bivia, P. buccae, P. disiens)

Susceptibility Testing

For specific information regarding susceptibility test interpretive criteria and associated test methods and quality control standards recognized by FDA for this drug, please see: https://www.fda.gov/STIC.

13 NONCLINICAL TOXICOLOGY

13.1 Carcinogenesis, Mutagenesis, Impairment of Fertility

Carcinogenesis

Tumors affecting the liver, lungs, mammary, and lymphatic tissues have been detected in several studies of metronidazole in rats and mice, but not hamsters. Pulmonary tumors have been observed in all six reported studies in the mouse, including one study in which the animals were dosed on an intermittent schedule (administration during every fourth week only). Malignant liver tumors were increased in male mice treated at approximately 1,500 mg/m^2(similar to the maximum recommended daily dose, based on body surface area comparisons). Malignant lymphomas and pulmonary neoplasms were also increased with lifetime feeding of the drug to mice. Mammary and hepatic tumors were increased among female rats administered oral metronidazole compared to concurrent controls. Two lifetime tumorigenicity studies in hamsters have been performed and reported to be negative.

Mutagenesis

Metronidazole has shown mutagenic activity in in vitro assay systems including the Ames test. Studies in mammals in vivo have failed to demonstrate a potential for genetic damage.

Impairment of Fertility

Metronidazole failed to produce any adverse effects on fertility or testicular function in male rats at doses up at 400 mg/kg/day (similar to the maximum recommended clinical dose, based on body surface area comparisons) for 28 days. However, rats treated at the same dose for 6 weeks or longer were infertile and showed severe degeneration of the seminiferous epithelium in the testes as well as marked decreases in testicular spermatid counts and epididymal sperm counts. Fertility was restored in most rats after an eight-week, drug-free recovery period.

16 HOW SUPPLIED/STORAGE AND HANDLING

How Supplied

LIKMEZ 500 mg/5 mL is a white to slightly brown suspension with characteristic strawberry peppermint flavor packed in white HDPE round bottles with a child-resistant cap and supplied as follows:

NDC 71656-066-75 Bottles of 75 mL

NDC 71656-066-20 Bottles of 200 mL

Storage

Store between 20°C to 25°C (68°F to 77°F). Brief exposure to 15°C to 30°C (59°F to 86°F) permitted [See USP Controlled Room Temperature]. Do not freeze.

Dispense in a tight container as defined in USP. Discard 60 days after opening container.

17 PATIENT COUNSELING INFORMATION

Advise the patient to read the FDA-approved patient labeling (Patient Information).

Administration Instructions

Instruct the patients and caregivers to:
• Ensure the prescribed dose of LIKMEZ oral suspension is taken as directed [ see Dosage and Administration (2)].
• Use a calibrated oral dosing device to correctly measure the prescribed dose of medication. Do not use a household teaspoon or tablespoon to measure doses. Calibrated oral dosing devices may be obtained from the pharmacy.
• Shake LIKMEZ oral suspension well before use each time.

Severe Cutaneous Adverse Reactions

Advise patients that LIKMEZ may increase the risk of serious and sometimes fatal dermatologic reactions, including toxic epidermal necrolysis (TEN), Stevens-Johnson syndrome (SJS), and drug reaction with eosinophilia and systemic symptoms (DRESS). Instruct the patient to be alert for skin rash, blisters, fever or other signs and symptoms of these hypersensitivity reactions. Advise patients to stop LIKMEZ immediately if they develop any type of rash and seek medical attention [ see Warnings and Precautions (5.2)] .

Alcohol or Products Containing Propylene Glycol

Advise patients to avoid consumption of alcoholic beverages and preparations containing ethanol or propylene glycol during LIKMEZ therapy and for 3 days afterward because abdominal cramps, nausea, vomiting, headaches, and flushing may occur [ see Contraindications (4.3)and Drug Interactions (7.2)] .

Lactation

Advise lactating women that they may choose to pump and discard human milk for the duration of LIKMEZ therapy and for 48 hours after the last dose and feed her infant stored human milk or formula [see Use in Specific Populations (8.2)] .

Central and Peripheral Nervous System Effects

Inform patients of the risk of central and peripheral nervous system effects while taking LIKMEZ. Advise patients to stop taking LIKMEZ and report immediately to their healthcare provider if any neurological symptoms occur [see Warnings and Precautions (5.3)] .

Drug Interactions

Advise patients to report the use of any other medications while taking LIKMEZ. Theadministration of any of the following drugs with LIKMEZ may result in clinically significant adverse reactions or reduced effectiveness of the drug [see Contraindications (4.2)and Drug Interactions (7.1to 7.7)] :

- Disulfiram
- Warfarin and other oral Anticoagulants
- Lithium
- Busulfan
- Cimetidine
- Phenytoin and Phenobarbital

Antibacterial Resistance
Patients should be counseled that antibacterial drugs including LIKMEZ should only be usedto treat bacterial infections. They do not treat viral infections (e.g., the common cold). WhenLIKMEZ is prescribed to treat a bacterial infection, patients should be told that although it is common to feel better early in the course of therapy, the medication should be taken exactly as directed. Skipping doses or not completing the full course of therapy may (1) decrease the effectiveness of the immediate treatment and (2) increase the likelihood that bacteria will develop resistance and will not be treatable by LIKMEZ or other antibacterial drugs in the future.

Distributed by:
Saptalis Pharmaceuticals LLC
Hauppauge, NY 11788
Made in USA

PATIENT INFORMATION

LIKMEZ®(lik mez)

(metronidazole)

oral suspension

What is LIKMEZ?

LIKMEZ is an antibiotic medicine used to treat:

- trichomoniasis (a sexually transmitted infection) in adults
- amebiasis (an infection caused by a parasite) in adults and children
- anaerobic bacterial infections (infections caused by bacteria that do not need oxygen to survive) in adults

It is not known if LIKMEZ is safe and effective in children, except for the treatment of amebiasis.

Do not take LIKMEZ if you:

- are allergic to metronidazole or other nitroimidazole medicines.
- have taken disulfiram (medicine used to help people stop drinking alcohol) in the last 2 weeks. Taking LIKMEZ with disulfiram can cause psychotic symptoms (seeing or hearing things that are not really there) in people who drink alcohol.
- drink alcohol or use products with propylene glycol during treatment with LIKMEZ and for at least 3 days after you stop taking LIKMEZ, because this can cause side effects including abdominal cramps, nausea, vomiting, headaches, and flushing.
- have Cockayne Syndrome (a rare genetic disorder that affects growth and development).

Before taking LIKMEZ, tell your healthcare provider about all of your medical conditions, including if you:

- have liver problems.
- have kidney problems.
- have medical problems that affect the brain.
- have a yeast infection.
- have a history of blood problems.
- are breastfeeding or plan to breastfeed. LIKMEZ can pass into your breastmilk. Talk to your healthcare provider about the best way to feed your baby while taking LIKMEZ. If you are breastfeeding, you may consider pumping and throwing away your breast milk during treatment with LIKMEZ and for 48 hours after your last dose of LIKMEZ and feeding your infant stored human milk or formula.

Tell your healthcare provider about all the medicines you take, including prescription and over-the-counter medicines, vitamins and herbal supplements. LIKMEZ and other medicines can affect each other causing side effects.

Especially tell your healthcare provider if you take:

- warfarin or other blood thinners (anticoagulants)
- lithium
- busulfan
- cimetidine
- phenytoin and phenobarbital

You can ask your pharmacist for a list of medicines that interact with LIKMEZ.

Know the medicines you take. Keep a list of them to show your healthcare provider and pharmacist when you get a new medicine.

How should I take LIKMEZ?

- Take LIKMEZ exactly as your healthcare provider tells you to.
- Shake LIKMEZ oral suspension well before each use.
- Always use an accurate measuring device to measure the correct amount of LIKMEZ. Do notuse a household teaspoon or tablespoon to measure your medicine. You can ask your pharmacist for the measuring device you should use and how to measure the correct dose.
- Do not skip any doses of LIKMEZ or stop taking it, even if you begin to feel better, until you have finished your prescribed treatment. Taking all of your LIKMEZ doses will help make sure that all of the bacteria are killed. Taking all of your LIKMEZ doses will help lower the chance that the bacteria will become resistant to LIKMEZ. If you become resistant to LIKMEZ, LIKMEZ and other antibacterial medicines may not work for you in the future.

If you take too much LIKMEZ, call your healthcare provider or go to the nearest emergency room right away.

What are the possible side effects of LIKMEZ?

LIKMEZ may cause serious side effects including:

- Severe skin reactions Serious skin reactions that may affect any part of the body and can lead to death, including toxic epidermal necrolysis (TEN), Stevens-Johnson Syndrome (SJS), drug reaction with eosinophilia and systemic symptoms (DRESS), and acute generalized exanthematous pustulosis (AGEP), have happened in some people taking metronidazole (the active ingredient in LIKMEZ). These severe skin reactions may be life threatening and you may need to be treated in a hospital. Stop taking LIKMEZ right away and call your healthcare provider or get emergency help if you have any of the following symptoms:

- skin rash or acne • blisters or sores in your mouth
- dry skin • peeling of your skin
- itching • fever
- blisters on your skin • muscle or joint aches
- redness or swelling of your face, hands, or soles of your feet • swollen glands

- Nervous system problems, including brain disorder (encephalopathy), inflammation of the brain and spinal cord membranes (aseptic meningitis), numbness or tingling in the hands or feet (peripheral neuropathy) and seizures (convulsions). Tell your healthcare provider right away if you have any nervous system problems while taking LIKMEZ.
- Worsening yeast infection (candidiasis) symptomsin people with a known yeast infection or a yeast infection they were not aware of.
- Low white blood cell count (leukopenia) in people with a history of blood problems. This can affect how well the body fights infection.

The most common side effects of LIKMEZ include: nausea, headache, anorexia, vomiting, diarrhea, pain in the upper abdomen, abdominal cramping, and constipation.

Other side effects of LIKMEZ include:

- allergic reactions: such as itching, hives (urticaria), flushing of the skin, red skin rash that can be widespread, blisters and separation of skin layers, nasal congestion, dryness of the mouth and vagina, and fever
- abnormal heart rhythm (QT prolongation)

These are not all the possible side effects of LIKMEZ. Call your doctor for medical advice about side effects. You may report side effects to FDA at 1‑800‑FDA-1088.

How should I store LIKMEZ?

- Store LIKMEZ oral suspension at room temperature between 68°F to 77°F (20°C to 25°C).
- Do not freeze.
- Throw away (discard) any unused LIKMEZ 60 days after opening the container.

Keep LIKMEZ and all medicines out of the reach of children.

General information about the safe and effective use of LIKMEZ.

Medicines are sometimes prescribed for purposes other than those listed in a Patient Information leaflet. Do not use LIKMEZ for a condition for which it was not prescribed. Do not give LIKMEZ to other people, even if they have the same symptoms that you have. It may harm them. You can ask your pharmacist or healthcare provider for information about LIKMEZ that is written for health professionals.

What are the ingredients in LIKMEZ?

Active ingredient:metronidazole

Inactive ingredients:glycerin, magnesium aluminum silicate, methylparaben, microcrystalline cellulose, natural peppermint flavor, natural strawberry flavor, propylparaben, purified water, sodium phosphate dibasic, sodium phosphate monobasic, sucralose, and sucrose.

Manufactured by:

Saptalis Pharmaceuticals LLC

Hauppauge, NY 11788

Made in USA

For more information, call 1-833-727-8254.

This Patient Information has been approved by the U.S. Food and Drug Administration.

Issued: 07/2024

Princial Display Panel

71656-066-20

LIKMEZ®

(metronidazole) Oral Supension

500 mg/mL

(100 mg/mL)

Strawberry Peppermint Flavor

For Oral Use Only

Rx only

200 mL

71656-066-75

LIKMEZ®

(metronidazole) Oral Supension

500 mg/mL

(100 mg/mL)

Strawberry Peppermint Flavor

For Oral Use Only

Rx only

75 mL